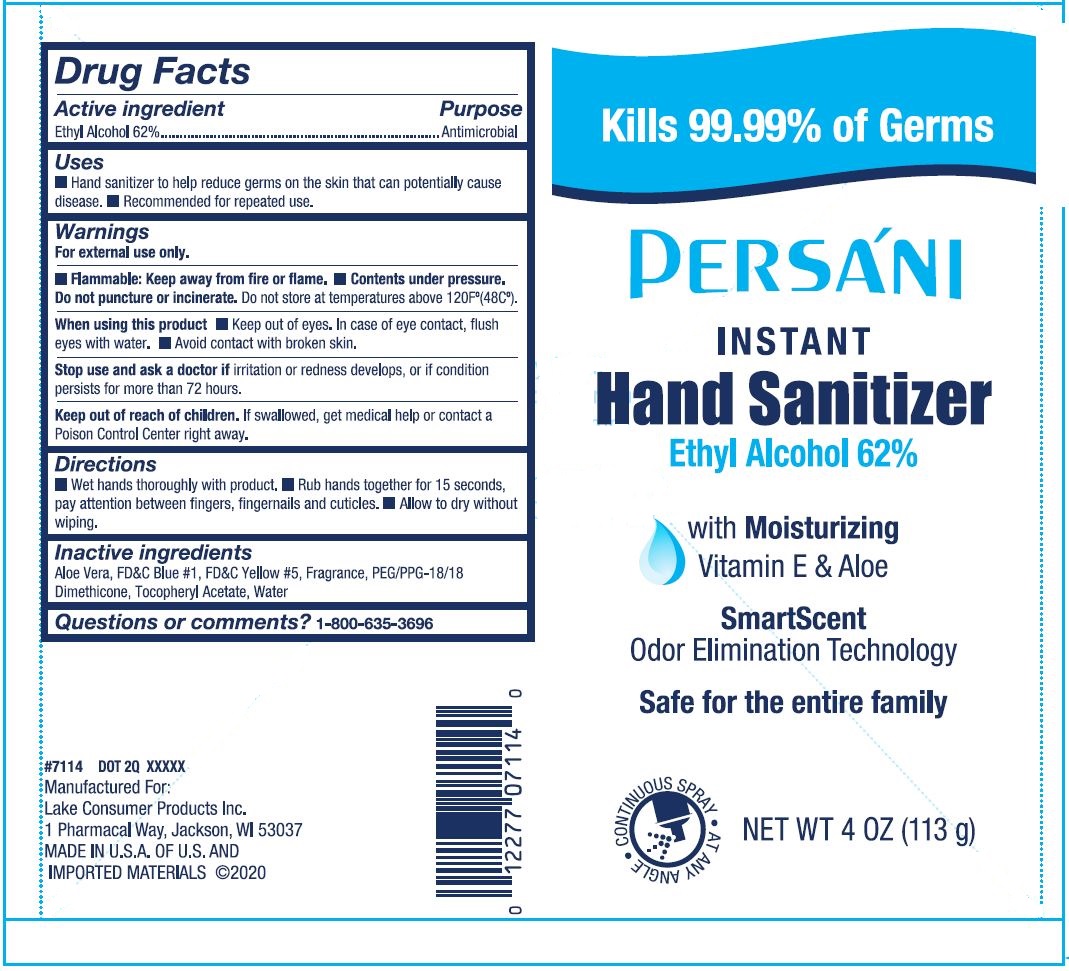 DRUG LABEL: Persani Hand Sanitizer
NDC: 68093-7114 | Form: SPRAY
Manufacturer: Wisconsin Pharmacal Company
Category: otc | Type: HUMAN OTC DRUG LABEL
Date: 20220113

ACTIVE INGREDIENTS: ALCOHOL 0.62 g/1 g
INACTIVE INGREDIENTS: FD&C YELLOW NO. 5; FD&C BLUE NO. 1; ALPHA-TOCOPHEROL ACETATE; WATER; PEG/PPG-18/18 DIMETHICONE; ALOE VERA LEAF

Persani Hand Sanitizer

Purpose

Hand Sanitizer to help reduce germs on the skin that can potentially cause disease.
Recomended for repeated use.

Drug Facts

Active Ingredient

Active ingredient | Purpose
Ethyl Alcohol 62% | Antimicrobial

Uses

- Hand Sanitizer to help reduce germs on the skin that can potentially cause disease.
- Recomended for repeated use.

Warnings

For external use only.

OTHER SAFETY INFORMATION

- Flammable: Keep away from fire or flame.
- Contents under pressure. Do not puncture or incinerate. Do not store at temperature above 120F°(48C°)

When using this product •Keep out of eyes. In case of eye contact, flush eyes with water.

•Avoid contact with broken skin.

Stop use and ask a doctor if irritation or redness develops, or if condition persists for more than 72 hours.

Keep out of reach of children. If swallowed, get medical help or contact a Poison Control Center right away.

Directions

- Wet hands throughly with product. Rub hands together for 15 seconds, pay attention between fingers, fingernails and cuticles.
- Allow to dry without wiping

Inactive ingredients

Aloe Vera, FD&C Blue #1, FD&C Yellow #5, Fragance, PEG/PPG-18/18 Dimethicone, Tocopheryl Acetate, Water

Questions or comments?

1-800-635-3696

Package Label - Principal Display Panel

Kills 99.99% of Germs

PERSANI

INSTANT

Hand Sanitizer

Ethyl Alcohol 62%

with Moisturizing

Vitamin E & Aloe

SmartScent

Odor Elimination Technology

Safe for the entire family

CONTINUOUS SPRAY

AT ANY ANGLE

NET WT 4 OZ (113 g)